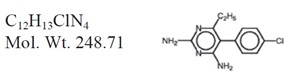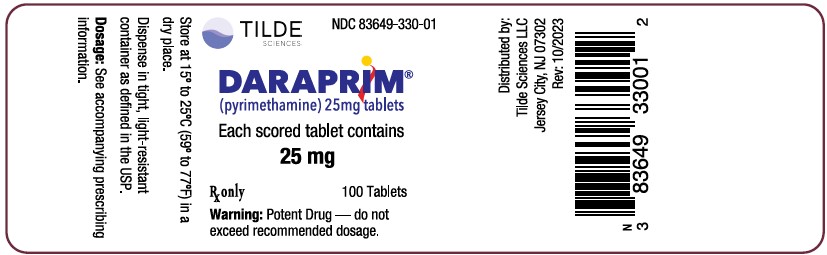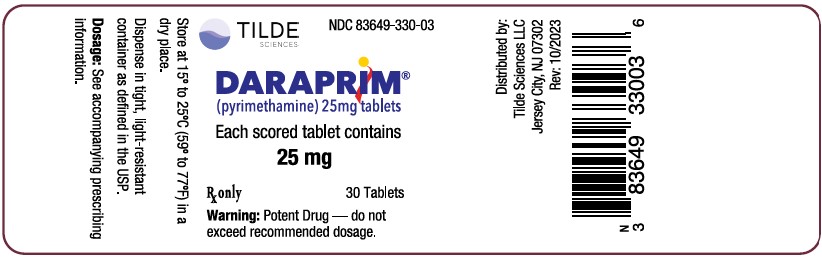 DRUG LABEL: Daraprim
NDC: 83649-330 | Form: TABLET
Manufacturer: TILDE Sciences LLC
Category: prescription | Type: HUMAN PRESCRIPTION DRUG LABEL
Date: 20231207

ACTIVE INGREDIENTS: PYRIMETHAMINE 25 mg/1 1
INACTIVE INGREDIENTS: STARCH, CORN; STARCH, POTATO; LACTOSE, UNSPECIFIED FORM; MAGNESIUM STEARATE

DARAPRIM® (pyrimethamine)

DESCRIPTION

DARAPRIM (pyrimethamine) is an antiparasitic compound available in tablet form for oral administration. Each scored tablet contains 25 mg pyrimethamine and the inactive ingredients corn and potato starch, lactose, and magnesium stearate.

Pyrimethamine, known chemically as 5-(4- chlorophenyl)-6-ethyl-2, 4-pyrimidinediamine, has the following structural formula:

CLINICAL PHARMACOLOGY

Pyrimethamine is well absorbed with peak levels occurring between 2 to 6 hours following administration. It is eliminated slowly and has a plasma half-life of approximately 96 hours. Pyrimethamine is 87% bound to human plasma proteins.

MICROBIOLOGY

Microbiology: Pyrimethamine is a folic acid antagonist and the rationale for its therapeutic action is based on the differential requirement between host and parasite for nucleic acid precursors involved in growth. This activity is highly selective against Toxoplasma gondii.

The action of pyrimethamine against Toxoplasma gondii is greatly enhanced when used in conjunction with sulfonamides. This was demonstrated by Eyles and Coleman^1 in the treatment of experimental toxoplasmosis in the mouse. Jacobs et al^2 demonstrated that combination of the 2 drugs effectively prevented the development of severe uveitis in most rabbits following the inoculation of the anterior chamber of the eye with toxoplasma.

INDICATIONS AND USAGE

Treatment of Toxoplasmosis: DARAPRIM is indicated for the treatment of toxoplasmosis when used conjointly with a sulfonamide, since synergism exists with this combination.

CONTRAINDICATIONS

Use of DARAPRIM is contraindicated in patients with known hypersensitivity to pyrimethamine or to any component of the formulation. Use of the drug is also contraindicated in patients with documented megaloblastic anemia due to folate deficiency.

WARNINGS

The dosage of pyrimethamine required for the treatment of toxoplasmosis has a narrow therapeutic window. If signs of folate deficiency develop (see ADVERSE REACTIONS), reduce the dosage or discontinue the drug according to the response of the patient. Folinic acid (leucovorin) should be administered in a dosage of 5 to 15 mg daily (orally, IV, or IM) until normal hematopoiesis is restored.
Data in 2 humans indicate that pyrimethamine may be carcinogenic; a 51-year-old female who developed chronic granulocytic leukemia after taking pyrimethamine for 2 years for toxoplasmosis^3 and a 56-year-old patient who developed reticulum cell sarcoma after 14 months of pyrimethamine for toxoplasmosis.^4

Pyrimethamine has been reported to produce a significant increase in the number of lung tumors in mice when given intraperitoneally at doses of 25 mg/kg.^5

DARAPRIM should be kept out of the reach of infants and children as they are extremely susceptible to adverse effects from an overdose. Deaths in pediatric patients have been reported after accidental ingestion.

PRECAUTIONS

GENERAL PRECAUTIONS

General: A small "starting" dose for toxoplasmosis is recommended in patients with convulsive disorders to avoid the potential nervous system toxicity of pyrimethamine. DARAPRIM should be used with caution in patients with impaired renal or hepatic function or in patients with possible folate deficiency, such as individuals with malabsorption syndrome, alcoholism, or pregnancy, and those receiving therapy, such as phenytoin, affecting folate levels (see Pregnancy subsection).

PATIENT COUNSELING INFORMATION

Information for Patients: Patients should be warned that at the first appearance of a skin rash they should stop use of DARAPRIM and seek medical attention immediately. Patients should also be warned that the appearance of sore throat, pallor, purpura, or glossitis may be early indications of serious disorders which require treatment with DARAPRIM to be stopped and medical treatment to be sought.
Women of childbearing potential who are taking DARAPRIM should be warned against becoming pregnant Patients should be warned to keep DARAPRIM out of the reach of children. Patients should be advised not to exceed recommended doses. Patients should be warned that if anorexia and vomiting occur, they may be minimized by taking the drug with meals. Concurrent administration of folinic acid is strongly recommended when used for the treatment of toxoplasmosis in all patients.

LABORATORY TESTS

Laboratory Tests: In patients receiving high dosage, semiweekly blood counts, including platelet counts, should be performed.

DRUG INTERACTIONS

Drug Interactions: Pyrimethamine may be used with sulfonamides, quinine and other antimalarials, and with other antibiotics. However, the concomitant use of other antifolic drugs or agents associated with myelosuppression including sulfonamides or trimethoprim- sulfamethoxazole combinations, proguanil, zidovudine, or cytostatic agents (e.g., methotrexate), while the patient is receiving pyrimethamine, may increase the risk of bone marrow suppression. If signs of folate deficiency develop, pyrimethamine should be discontinued. Folinic acid (leucovorin) should be administered until normal hematopoiesis is restored (see WARNINGS). Mild hepatotoxicity has been reported in some patients when lorazepam and pyrimethamine were administered concomitantly.

CARCINOGENESIS AND MUTAGENESIS AND IMPAIRMENT OF FERTILITY

Carcinogenesis, Mutagenesis, Impairment of Fertility: See WARNINGS section for information on carcinogenesis.

Mutagenesis: Pyrimethamine has been shown to be nonmutagenic in the following in vitro assays: the Ames point mutation assay, the Rec assay, and the E. coli WP2 assay. It was positive in the L5178Y/ TK +/- mouse lymphoma assay in the absence of exogenous metabolic activation.^6 Human blood lymphocytes cultured in vitro had structural chromosome aberrations induced by pyrimethamine. In vivo, chromosomes analyzed from the bone marrow of rats dosed with pyrimethamine showed an increased number of structural and numerical aberrations.

PREGNANCY

Pregnancy: Teratogenic Effects: Pregnancy Category C. Pyrimethamine has been shown to be teratogenic in rats when given in oral doses 2.5 times the human dose for treatment of toxoplasmosis. At these doses in rats, there was a significant increase in abnormalities such as cleft palate, brachygnathia, oligodactyly, and microphthalmia. Pyrimethamine has also been shown to produce terata such as meningocele in hamsters and cleft palate in miniature pigs when given in oral doses 5 times the human dose for the treatment of toxoplasmosis.

There are no adequate and well-controlled studies in pregnant women. DARAPRIM should be used during pregnancy only if the potential benefit justifies the potential risk to the fetus.

Concurrent administration of folinic acid is strongly recommended when used during pregnancy.

NURSING MOTHERS

Nursing Mothers: Pyrimethamine is excreted in human milk. Because of the potential for serious adverse reactions in nursing infants from pyrimethamine and from concurrent use of a sulfonamide with DARAPRIM for treatment of some patients with toxoplasmosis, a decision should be made whether to discontinue nursing or to discontinue the drug, taking into account the importance of the drug to the mother (see WARNINGS and PRECAUTIONS: Pregnancy).

Pediatric Use: See DOSAGE AND ADMINISTRATION section.

GERIATRIC USE

Geriatric Use: Clinical studies of DARAPRIM did not include sufficient numbers of subjects aged 65 and over to determine whether they respond differently from younger subjects. Other reported clinical experience has not identified differences in responses between the elderly and younger patients. In general, dose selection for an elderly patient should be cautious, usually starting at the low end of the dosing range, reflecting the greater frequency of decreased hepatic, renal, or cardiac function, and of concomitant disease or other drug therapy.

ADVERSE REACTIONS

Hypersensitivity reactions, occasionally severe (such as Stevens- Johnson syndrome, toxic epidermal necrolysis, erythema multiforme, and anaphylaxis), and hyperphenylalaninemia, can occur particularly when pyrimethamine is administered concomitantly with a sulfonamide. Consult the complete prescribing information for the relevant sulfonamide for sulfonamide-associated adverse events. With doses of pyrimethamine used for the treatment of toxoplasmosis, anorexia and vomiting may occur. Vomiting may be minimized by giving the medication with meals; it usually disappears promptly upon reduction of dosage. Doses used in toxoplasmosis may produce megaloblastic anemia, leukopenia, thrombocytopenia, pancytopenia, neutropenia, atrophic glossitis, hematuria, and disorders of cardiac rhythm.

Hematologic effects, however, may also occur at low doses in certain individuals (see PRECAUTIONS; General).

Pulmonary eosinophilia has been reported rarely.

OVERDOSAGE

Following the ingestion of 300 mg or more of pyrimethamine, gastrointestinal and/or central nervous system signs may be present, including convulsions. The initial symptoms are usually gastrointestinal and may include abdominal pain, nausea, severe and repeated vomiting, possibly including hematemesis. Central nervous system toxicity may be manifest by initial excitability, generalized and prolonged convulsions which may be followed by respiratory depression, circulatory collapse, and death within a few hours. Neurological symptoms appear rapidly (30 minutes to 2 hours after drug ingestion), suggesting that in gross overdosage pyrimethamine has a direct toxic effect on the central nervous system.

The fatal dose is variable, with the smallest reported fatal single dose being 375 mg. There are, however, reports of pediatric patients who have recovered after taking 375 to 625 mg.

There is no specific antidote to acute pyrimethamine poisoning. In the event of overdosage, symptomatic and supportive measures should be employed. Gastric lavage is recommended and is effective if earned out very soon after drug ingestion. Parenteral diazepam may be used to control convulsions. Folinic acid should be administered within 2 hours of drug ingestion to be most effective in counteracting the effects on the hematopoietic system (see WARNINGS). Due to the long half-life of pyrimethamine, daily monitoring of peripheral blood counts is recommended for up to several weeks after the overdose until normal hematologic values are restored.

DOSAGE AND ADMINISTRATION

For Treatment of Toxoplasmosis: The dosage of DARAPRIM for the treatment of toxoplasmosis must be carefully adjusted so as to provide maximum therapeutic effect and a minimum of side effects. At the dosage required, there is a marked variation in the tolerance to the drug. Young patients may tolerate higher doses than older individuals. Concurrent administration of folinic acid is strongly recommended in all patients.

The adult starting dose is 50 to 75 mg of the drug daily, together with 1 to 4 g daily of a sulfonamide of the sulfapyrimidine type, e.g. sulfadoxine. This dosage is ordinarily continued for 1 to 3 weeks, depending on the response of the patient and tolerance to therapy. The dosage may then be reduced to about one half that previously given for each drug and continued for an additional 4 to 5 weeks. The pediatric dosage of DARAPRIM is 1 mg/kg/day divided into 2 equal daily doses; after 2 to 4 days this dose may be reduced to one half and continued for approximately 1 month. The usual pediatric sulfonamide dosage is used in conjunction with DARAPRIM.

HOW SUPPLIED:

White, scored tablets containing 25 mg pyrimethamine, imprinted with “DARAPRIM” and “A3A" in bottles of 100 (NDC 83649-330-01) and bottles of 30 (NDC 83649 -330-03).

Store at 15° to 25°C (59° to 77°F) in a dry place and protect from light

REFERENCES

1. Eyles DE, Coleman N. Synergistic effect of sulfadiazine and Daraprim against experimental toxoplasmosis in the mouse. Antibiot Chemother 1953;3:483-490.
2. Jacobs L, Melton ML, Kaufman HE. Treatment of experimental ocular toxoplasmosis. Arch Ophthalmol. 1964;71:111 -118.
3. Jim RTS, Elizaga FV. Development of chronic granulocytic leukemia in a patient treated with pyrimethamine. Hawaii Med J. 1977;36:173-176.
4. Sadoff L. Antimalarial drugs and Burkitt's lymphoma. Lancet. 1973;2:1262-1263.
5. Bahna L. Pyrimethamine. LARC Monogr Eval Carcinog Risk Chem. 1977;13:233-242.
6. Clive D, Johnson KO, Specter JKS, et al. Validation and characterization of the L5178Y/TK +/- mouse lymphoma mutagen assay system. Mut Res. 1979;59:61-108.

Distributed by: Tilde Sciences LLC
Jersey City NJ 07302
Rev. 10/2023

Principal Display Panel - Daraprim 100 Tablets Bottle Label

TILDE NDC 83649-330-01
Sciences
DARAPRIM®
(pyrimethamine) 25mg tablets
Each scored tablet contains
25 mg
Rx only 100 Tablets
Warning: Potent Drug - do not
exceed recommended dosage.
Store at 15° to 25°C (59° to 77°F) in a
dry place.
Dispense in tight, light-resistant
container as defined in the USP.
Dosage: See accompanying prescribing
information.
Distributed by:
Tilde Sciences LLC
Jersey City, NJ 07302
Rev: 10/2023

Principal Display Panel - Daraprim 30 Tablets Bottle Label

TILDE NDC 83649-330-03
Sciences
DARAPRIM®
(pyrimethamine) 25mg tablets
Each scored tablet contains
25 mg
Rx only 30 Tablets
Warning: Potent Drug - do not
exceed recommended dosage.
Store at 15° to 25°C (59° to 77°F) in a
dry place.
Dispense in tight, light-resistant
container as defined in the USP.
Dosage: See accompanying prescribing
information.
Distributed by:
Tilde Sciences LLC
Jersey City, NJ 07302
Rev: 10/2023